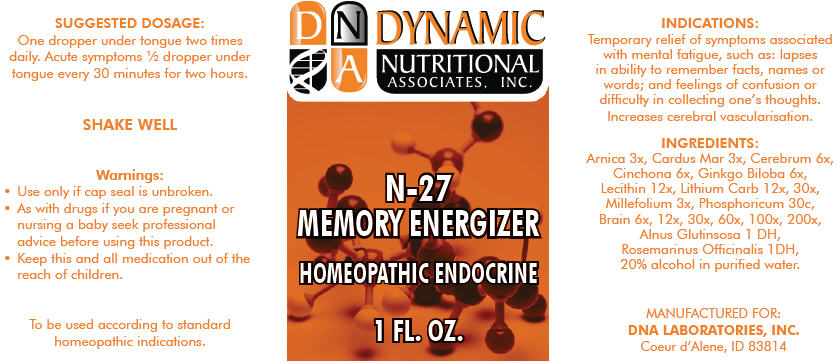 DRUG LABEL: N-27
NDC: 58264-0225 | Form: SOLUTION
Manufacturer: DNA Labs, Inc.
Category: homeopathic | Type: HUMAN OTC DRUG LABEL
Date: 20250109

ACTIVE INGREDIENTS: ARNICA MONTANA 3 [hp_X]/1 mL; MILK THISTLE 3 [hp_X]/1 mL; SUS SCROFA CEREBRUM 6 [hp_X]/1 mL; CINCHONA OFFICINALIS BARK 6 [hp_X]/1 mL; GINKGO BILOBA WHOLE 6 [hp_X]/1 mL; LECITHIN, SOYBEAN 12 [hp_X]/1 mL; LITHIUM CARBONATE 30 [hp_X]/1 mL; ACHILLEA MILLEFOLIUM 3 [hp_X]/1 mL; PHOSPHORIC ACID 30 [hp_X]/1 mL; PORK BRAIN 200 [hp_X]/1 mL; ALNUS GLUTINOSA WHOLE 1 [hp_X]/1 mL; ROSMARINUS OFFICINALIS FLOWERING TOP 1 [hp_X]/1 mL
INACTIVE INGREDIENTS: ALCOHOL; WATER

N-27

INDICATIONS

PURPOSE

Temporary relief of symptoms associated with mental fatigue, such as: lapses in ability to remember facts, names or words; and feelings of confusion or difficulty in collecting one's thoughts. Increases cerebral vascularisation.

INGREDIENTS

INACTIVE INGREDIENT

Arnica 3x, Cardus Mar 3x, Cerebrum 6x, Cinchona 6x, Ginkgo Biloba 6x, Lecithin 12x, Lithium Carb 12x, 30x, Millefolium 3x, Phosphoricum 30c, Brain 6x, 12x, 30x, 60x, 100x, 200x, Alnus Glutinsosa 1 DH, Rosemarinus Officinalis 1DH, 20% alcohol in purified water.

SUGGESTED DOSAGE

One dropper under tongue two times daily. Acute symptoms ½ dropper under tongue every 30 minutes for two hours.

STORAGE AND HANDLING

SHAKE WELL

Warnings

- Use only if cap seal is unbroken.

PREGNANCY OR BREAST FEEDING

- As with drugs if you are pregnant or nursing a baby seek professional advice before using this product.

KEEP OUT OF REACH OF CHILDREN

- Keep this and all medication out of the reach of children.

To be used according to standard homeopathic indications.

PRINCIPAL DISPLAY PANEL - 1 FL. OZ. Bottle Label

DYNAMIC
NUTRITIONAL
ASSOCIATES, INC.

N-27
MEMORY ENERGIZER

HOMEOPATHIC ENDOCRINE

1 FL. OZ.